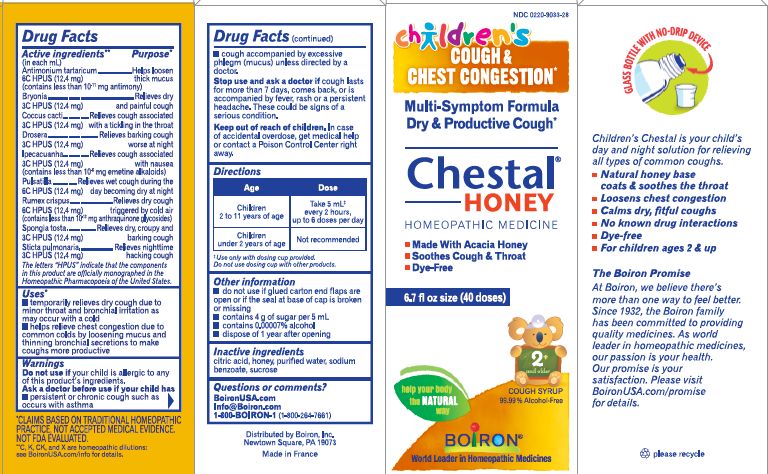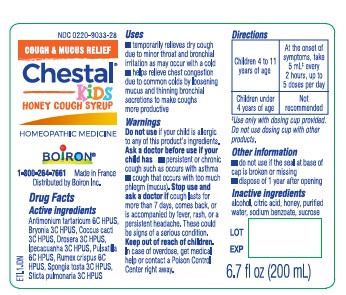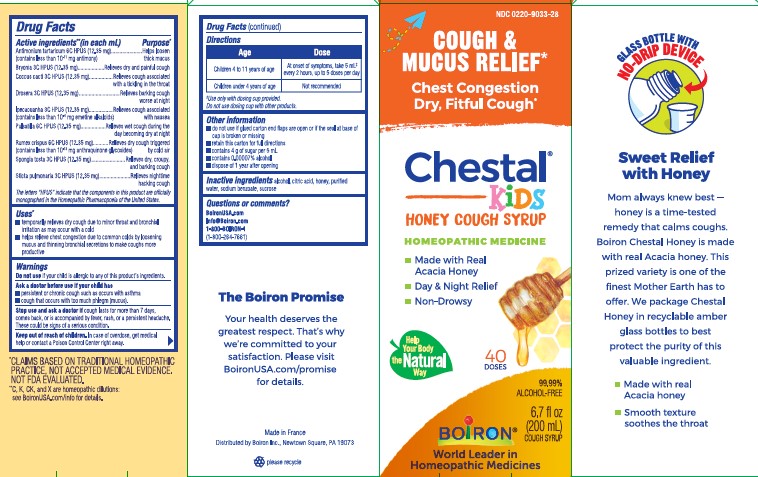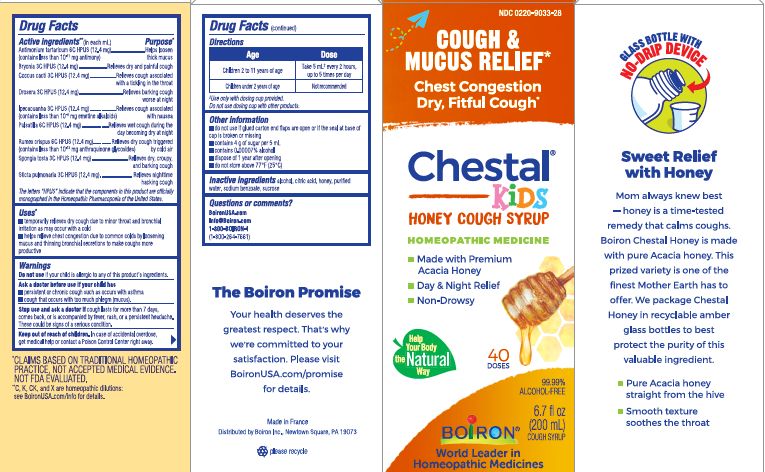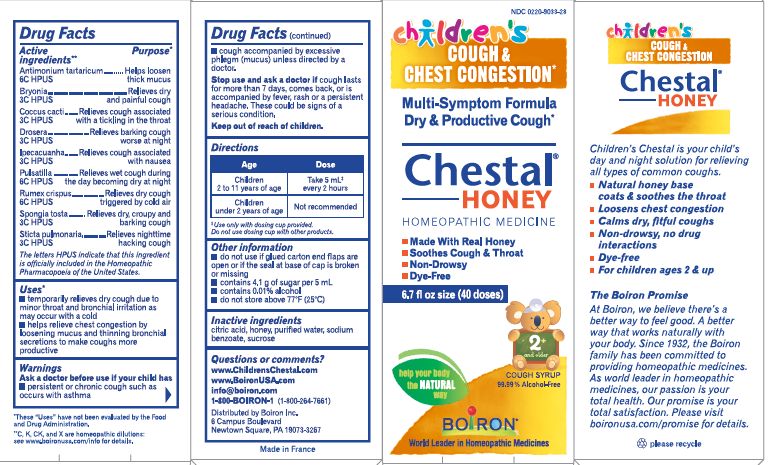 DRUG LABEL: Chestal for Children
NDC: 0220-9033 | Form: SYRUP
Manufacturer: Laboratoires Boiron
Category: homeopathic | Type: HUMAN OTC DRUG LABEL
Date: 20230718

ACTIVE INGREDIENTS: BRYONIA ALBA ROOT 3 [hp_C]/1 1; PROTORTONIA CACTI 3 [hp_C]/1 1; DROSERA ROTUNDIFOLIA FLOWERING TOP 3 [hp_C]/1 1; IPECAC 3 [hp_C]/1 1; PULSATILLA VULGARIS 6 [hp_C]/1 1; RUMEX CRISPUS ROOT 6 [hp_C]/1 1; SPONGIA OFFICINALIS SKELETON, ROASTED 3 [hp_C]/1 1; LOBARIA PULMONARIA 3 [hp_C]/1 1; ANTIMONY POTASSIUM TARTRATE 6 [hp_C]/1 1
INACTIVE INGREDIENTS: ALCOHOL; HONEY; SUCROSE; WATER; CITRIC ACID MONOHYDRATE; SODIUM BENZOATE

Chestal Child Honey

ACTIVE INGREDIENT

Antimonium tartaricum 6C HPUS (12.35 mg) (contains less than 10^-11 mg antimony)
Bryonia 3C HPUS (12.35 mg)
Coccus cacti 3C HPUS (12.35 mg)
Drosera 3C HPUS (12.35 mg)

Ipecacuanha 3C HPUS (12.35 mg) (contains less than 10^-6 mg emetine alkaloids)

Pulsatilla 6C HPUS (12.35 mg)
Rumex crispus 6C HPUS (12.35 mg) (contains less than 10^-13 mg anthraquinone glycosides)
Spongia tosta 3C HPUS (12.35 mg)
Sticta pulmonaria 3C HPUS (12.35 mg)

The letters "HPUS" indicate that the components in this product are officially monographed in the Homeopathic Parmacopoeia of the United States.

PURPOSE

Antimonium tartaricum 6C HPUS .. Helps loosen thick mucus
Bryonia 3C HPUS ... Relieves dry and painful cough
Coccus cacti 3C HPUS ... Relieves cough associated with a tickling in the throat
Drosera 3C HPUS ... Relieves barking cough worse at night
Ipecacuanha 3C HPUS ... Relieves cough associated with nausea
Pulsatilla 6C HPUS ... Relieves wet cough during the day becoming dry at night
Rumex crispus 6C HPUS ... Relieves dry cough triggered by cold air
Spongia tosta 3C HPUS ... Relieves dry, croupy and barking cough
Sticta pulmonaria 3C HPUS ... Relieves nighttime hacking cough

INDICATIONS AND USAGE

temporarily relieves dry cough due to minor throat and bronchial irritation as may occur with cold

helps relieve chest congestion due to common colds by loosening mucus and thinning bronchial secretions to make coughs more productive

Do not use if your child is allergic to any of this product's ingredients.

Ask a doctor before use if your child has

persistent or chronic cough such as occurs with asthma

cough that occurs with too much phlegm (mucus).

Stop use and ask a doctor if cough lasts for more than 7 days, comes back, or is accompanied by fever, rash, or a persistent headache. These could be a sign of a serious condition.

Keep out of reach of children. In case of accidental overdose, get medical help or contact a Poison Control Center right away.

Directions

Children 4 to 11 years of age - At the onset of symptoms, take 5mL^+ every 2 hours, up to 5 doses per day

Children under 4 years of age - Not recommended

^+ Use only with dosing cup provided.

Do not use dosing cup with other products.

do not use if glued carton end flaps are open or if the seal at base of cap is broken or missing

retain this carton for full directions

contains 4 g of sugar per 5 ml

contains 0.00007% alcohol

dispose 1 year after opening

6.7 fl oz (200 ml)

Cough & Mucus Relief*

Chest Congestion, Dry, Fitful Cough*

*CLAIMS BASED ON TRADITIONAL HOMEOPATHIC PRACTICE NOT ACCEPTED MEDICAL EVIDENCE. NOT FDA EVALUATED.

**C,K,CK, and X are homeopathic dilutions: see BoironUSA.com/info for details.

INACTIVE INGREDIENT

alcohol, citric acid, honey, purified water, sodium benzoate, sucrose

Questions, Comments
BoironUSA.com

info@boironusa.com
1-800-BOIRON-1 (1-800-264-7661)

Distributed by
Boiron Inc,
Newtown Square, PA 19073-3267